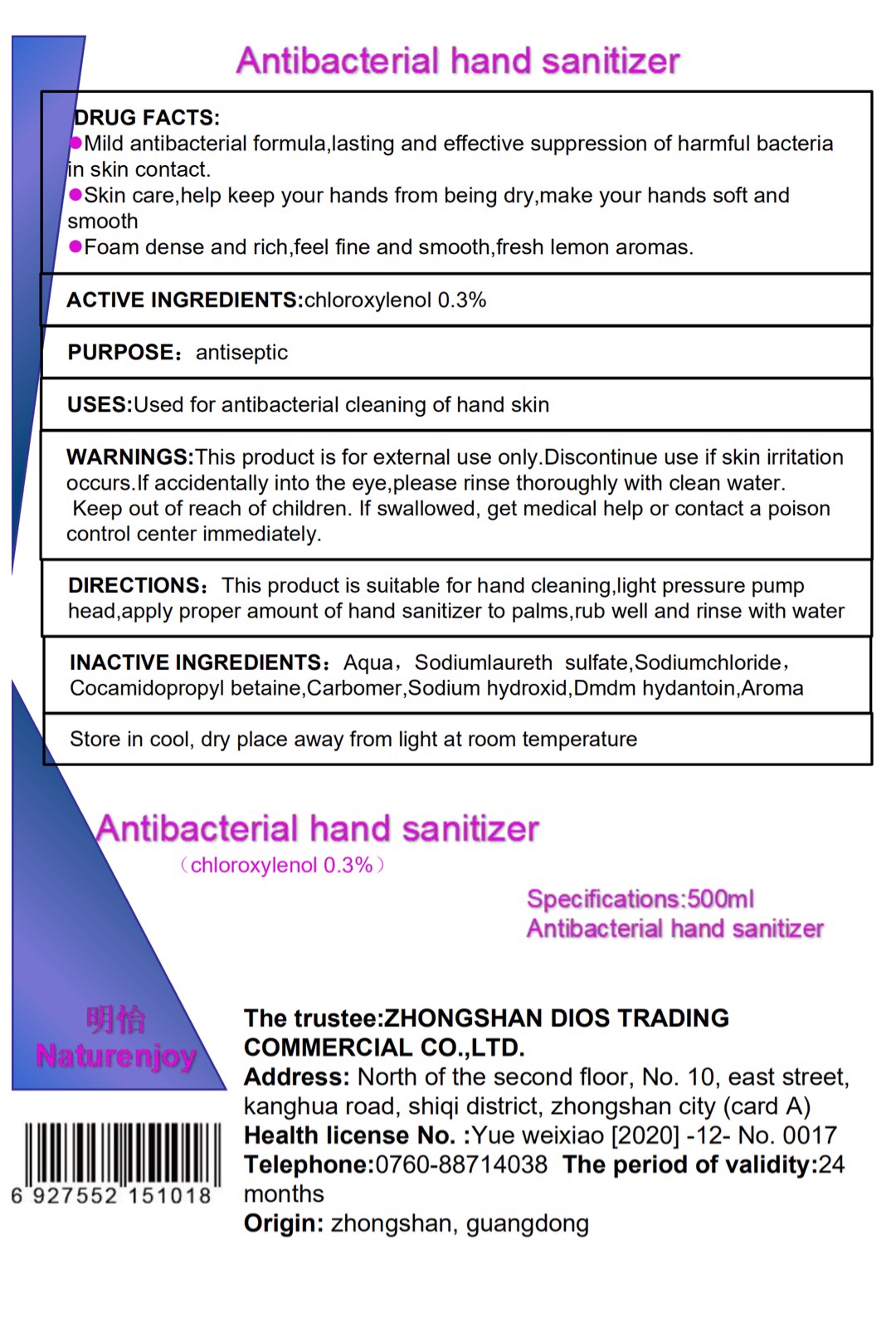 DRUG LABEL: Antibacterial Hand Sanitizer
NDC: 74532-001 | Form: SOLUTION
Manufacturer: ZHONGSHAN DIOS TRADING COMMERCIAL CO., LTD.
Category: otc | Type: HUMAN OTC DRUG LABEL
Date: 20200406

ACTIVE INGREDIENTS: CHLOROXYLENOL 0.3 g/100 mL
INACTIVE INGREDIENTS: SODIUM LAURETH SULFATE; SODIUM CHLORIDE; WATER; COCAMIDOPROPYL BETAINE; CARBOMER 934; SODIUM HYDROXIDE; DMDM HYDANTOIN

Drug Fact

Active Ingredient(s)

CHLOROXYLENOL: 0.3%. Purpose: Antiseptic

Purpose

Antiseptic

Use

Use: Used for antibacterial cleaning of hand skin

Warnings

Warning: For external use only. Discontinue use if skin irritation occurs. If accidentally into the eyes, please rinse thoroughly with clean water.

Keep out of reach of children. If swallowed, get medical help or contact a Poison Control Center immeidately.

DOSAGE AND ADMINISTRATION

Directions: This product is shuitable for hand cleaning. Light pressure pump head, apply proper amount of hand sanitizer into palms, rub well and rinse with water

Inactive ingredients

Inactive Ingredients: Water, Sodium Laureth Sulfate, Sodium Chloride, Cocamidopropyl Betaine, Carbomer, Sodium Hydroxide, DMDM Hydantoin, Aroma

STORAGE AND HANDLING

Storage: Store in cool dry place away from light at room temperature